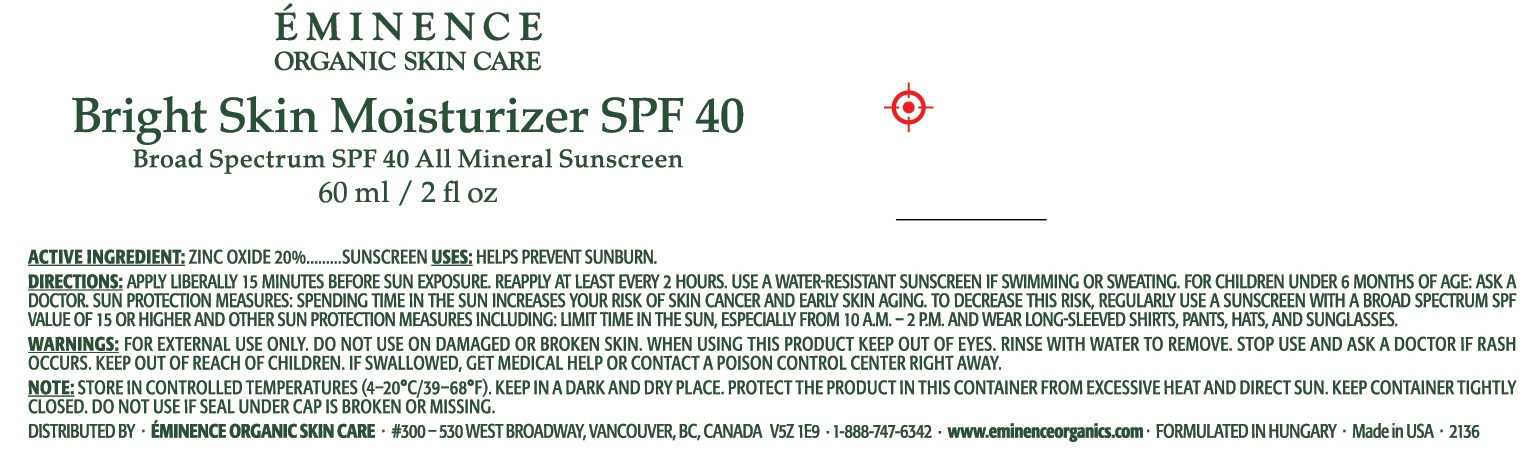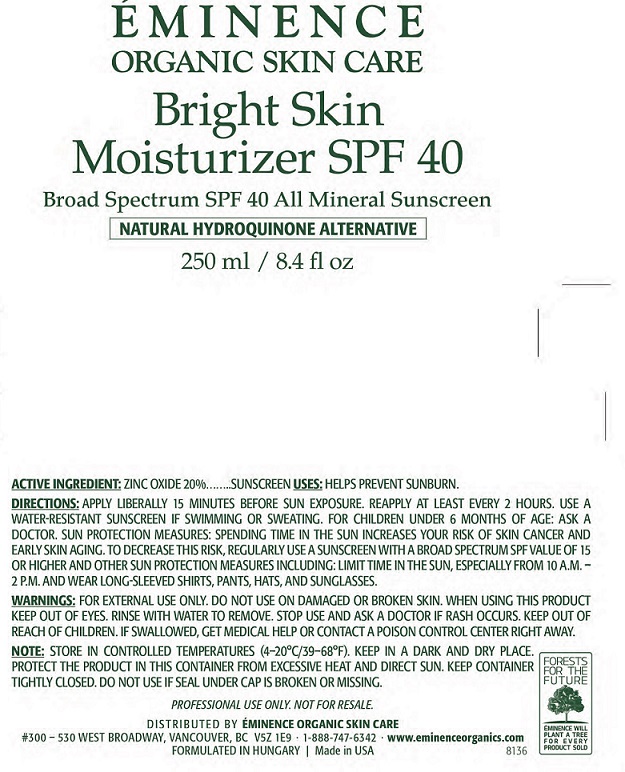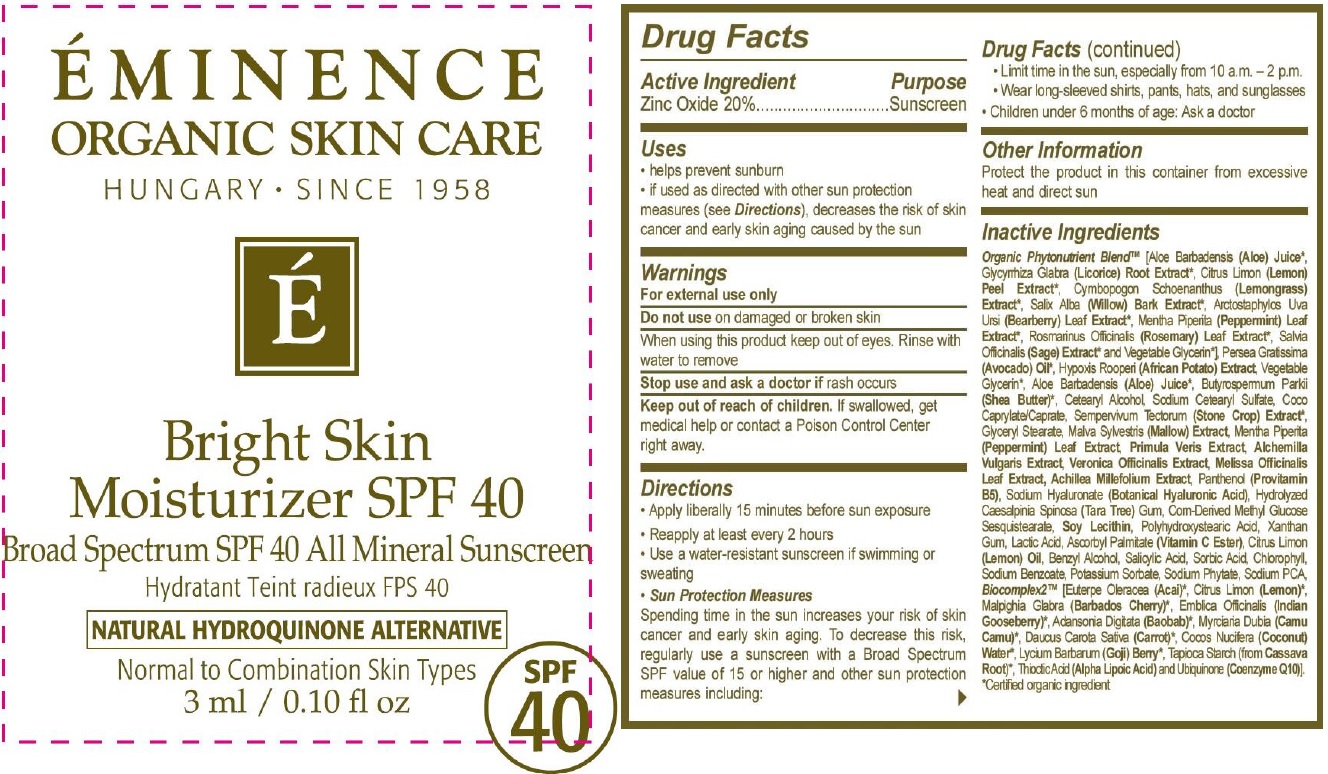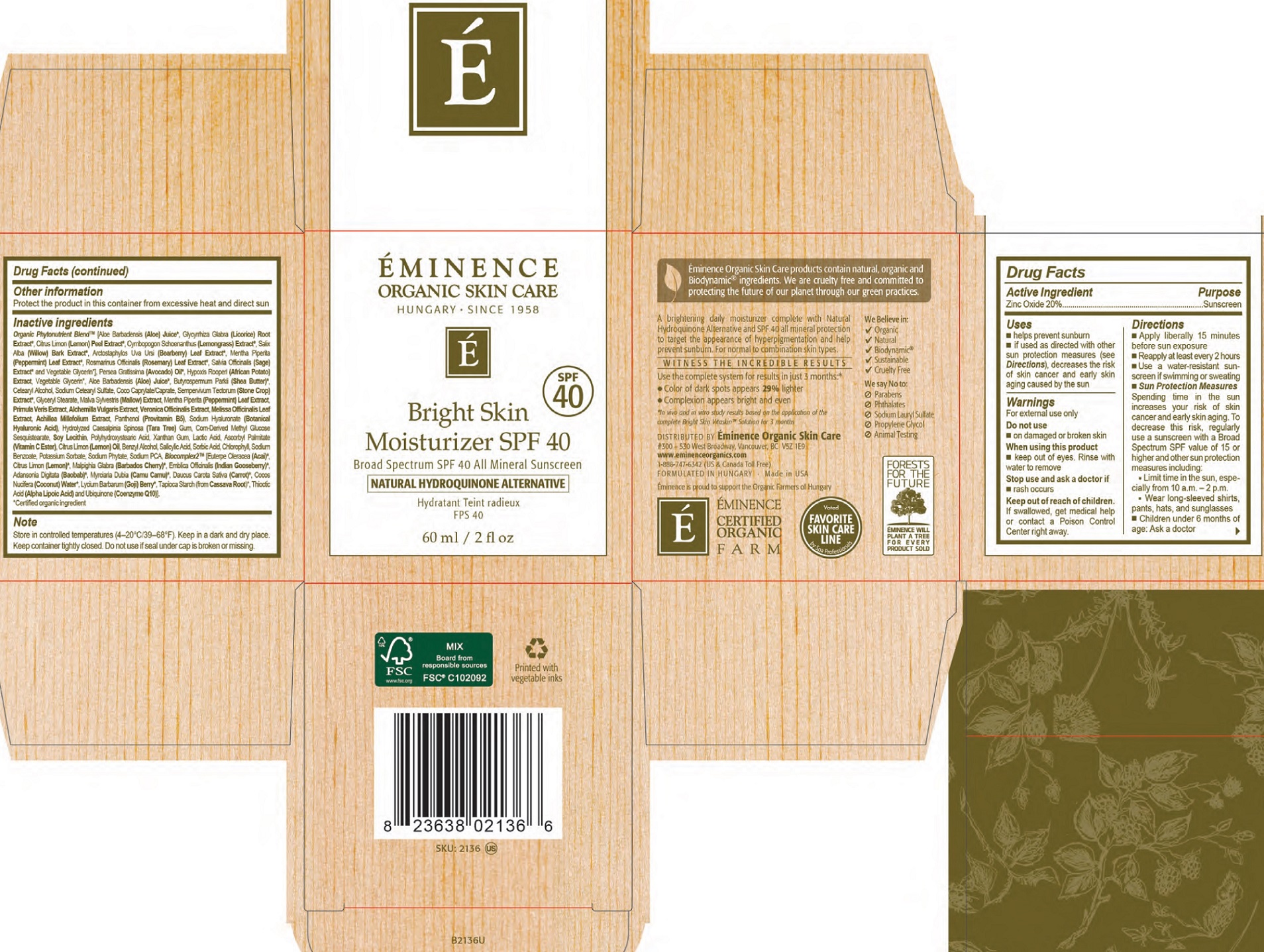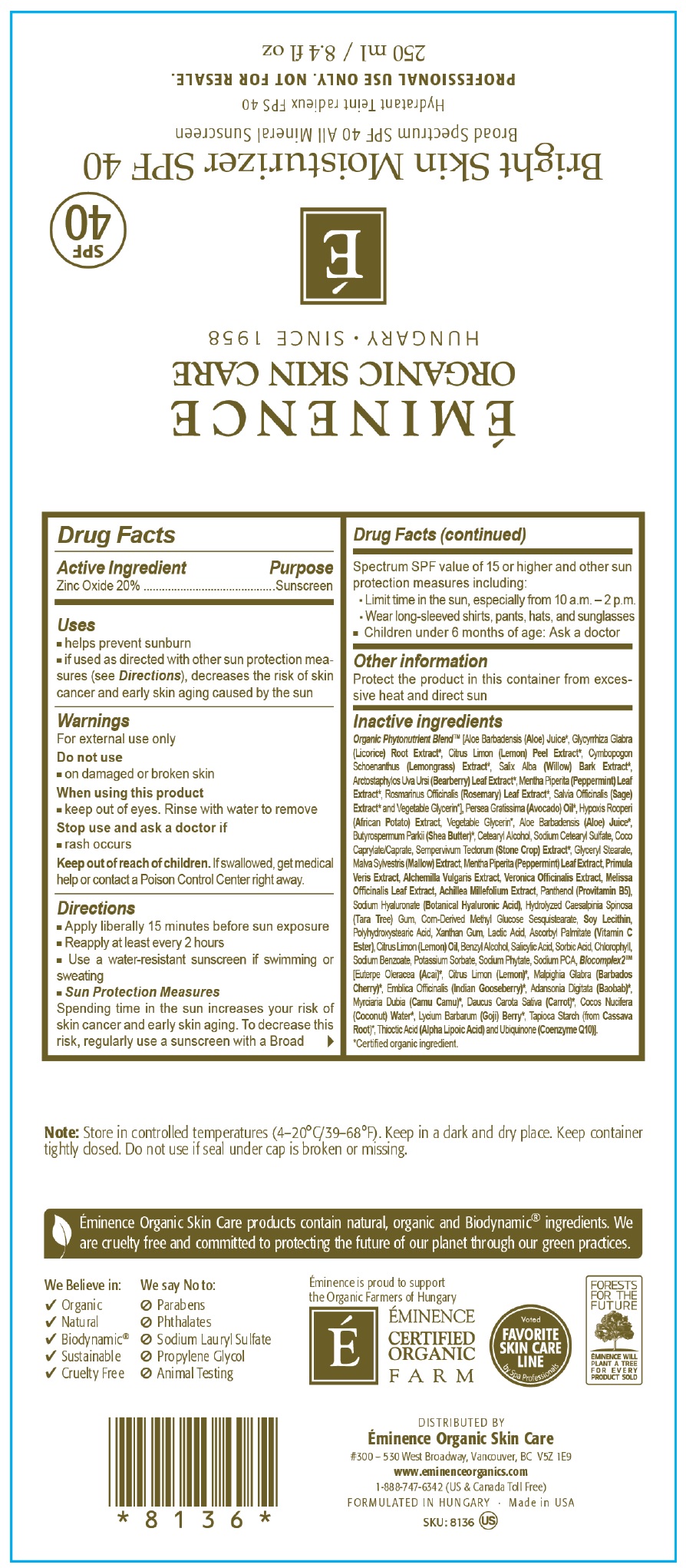 DRUG LABEL: Eminence Bright Skin Moisturizer SPF 40 Sunscreen
NDC: 15751-3503 | Form: CREAM
Manufacturer: Eminence Organic Skin Care
Category: otc | Type: HUMAN OTC DRUG LABEL
Date: 20231202

ACTIVE INGREDIENTS: ZINC OXIDE 200 mg/1 mL
INACTIVE INGREDIENTS: ALOE VERA LEAF; GLYCYRRHIZA GLABRA; LEMON; CYMBOPOGON SCHOENANTHUS TOP; SALIX ALBA BARK; ARCTOSTAPHYLOS UVA-URSI LEAF; MENTHA PIPERITA LEAF; ROSEMARY; SAGE; GLYCERIN; AVOCADO OIL; SHEA BUTTER; CETOSTEARYL ALCOHOL; SODIUM CETOSTEARYL SULFATE; COCOYL CAPRYLOCAPRATE; GLYCERYL MONOSTEARATE; MALVA SYLVESTRIS FLOWERING TOP; PRIMULA VERIS WHOLE; ALCHEMILLA XANTHOCHLORA FLOWERING TOP; MELISSA OFFICINALIS LEAF; ACHILLEA MILLEFOLIUM WHOLE; PANTHENOL; HYALURONATE SODIUM; LECITHIN, SOYBEAN; XANTHAN GUM; LACTIC ACID; ASCORBYL PALMITATE; BENZYL ALCOHOL; SALICYLIC ACID; SORBIC ACID; CHLOROPHYLL; SODIUM BENZOATE; POTASSIUM SORBATE; PHYTATE SODIUM; SODIUM PYRROLIDONE CARBOXYLATE; ACAI; CARROT; COCONUT WATER; STARCH, TAPIOCA; THIOCTIC ACID; UBIDECARENONE

Eminence Bright Skin Moisturizer SPF 40 Sunscreen

Active Ingredients

Zinc Oxide 20%

Purpose

Sunscreen

Uses

- helps prevent sunburn
- if used as directed with other sun protection measures (see Directions), decreases the risk of skin cancer and early skin aging caused by sun

Warnings

For external use only

Do not use

- on damaged or broken skin

When using this product

- keep out of eyes. Rinse with water to remove

Stop use and ask a doctor if

- rash occurs

Keep out of reach of children.

If swallowed, get medical help or contact a Poison Control Center right away.

Directions

- Apply liberally 15 minutes before sun exposure
- Reapply at least every 2 hours
- Use a water-resistant sunscreen if swimming or sweating
- Sun Protection Measures Spending time in the sun increases your risk of skin cancer and early skin aging. To decrease this risk, regularly use a sunscreen with a Broad Spectrum SPF value of 15 or higher and other sun protection measures including:
- Limit time in the sun, especially from 10 a.m. - 2 p.m/
- Wear long sleeved shirts, pants, hats and sunglasses
- Children under 6 months of age: Ask a doctor

Other information

Protect the product in this container from excessive heat and direct sun

Inactive Ingredients

Organic Phytonutrient Blend [Aloe Barbadensis (Aloe) Juice, Glycyrrhiza Glabra (Licorice) Root Extract*, Citrus Limon (Lemon) Peel Extract*, Cymbopogon Schoenanthus (Lemongrass) Extract*, Salix Alba (Willow) Bark Extract*, Arctostaphylos Uva Ursi (Bearberry) Leaf Extract*, Mentha Piperita (Peppermint) Leaf Extract, Rosmarinus Officinalis (Rosemary) Leaf Extract*, Salvia Officinalis (Sage) Extract*, and Vegetable Glycerin], Persea Gratissima (Avocado) Oil*, Hypoxis Rooperi (African Potato) Extract, Vegetable Glycerin*, Aloe Barbadensis (Aloe) Juice*, Butyrospermum Parkii (Shea Butter)*, Cetearyl Alcohol, Sodium Cetearyl Sulfate, Coco Caprylate/Caprate, Sempervivum Tectorum (Stone Crop) Extract*, Glyceryl Stearate, Malva Sylvestris (Mallow) Extract, Mentha Piperita (Peppermint) Leaf Extract, Primula Veris Extract, Alchemilla Vulgaris Extract, Veronica Officinalis Extract, Melissa Officinalis Leaf Extract, Achillea Millefolium Extract, Panthenol (Provitamin B5), Sodium Hyaluronate (Botanical Hyaluronic Acid), Hydrolyzed Caesalpinia Spinosa (Tara Tree) Gum, Com-Derived Methyl Glucose Sesquistearate, Soy Lecithin, Polyhydroxystaric Acid, Xanthan Gum, Lactic Acid, Ascorbyl Palmitate (Vitamin C Ester), Citrus Limon (Lemon) Oil, Benzyl Alcohol, Salicylic Acid, Sorbic Acid, Chlorophyl, Sodium Benzoate, Potassium Sorbate, Sodium Phytate, Sodium PCA, Blocomplex2 (Euterpe Oleracea (Acai)*, Citrus Limon (Lemon)*, Malpighia Glabra (Barbados Cherry)*, Embica Officinalis (Indian Gooseberry)*, Adansonia Digitata (Baobab)*, Myrciaria Dubia (Camu Camu)*, Daucus Carota Sativa (Carrot)*, Cocos Nucifera (Coconut) Water*, Lycium Barbarum (Goji) Berry*, Tapioca Starch (from Cassava Root)*, Thioctic Acid (Alpha Lipoic Acid) and Ubiquinone (Coenzyme Q10)].
*Certified organic ingredient

Note

Store in controlled temperatures (4–20°C/39–68°F). Keep in a dark and dry place. Keep container tightly closed. Do not use if seal under cap is broken or missing.